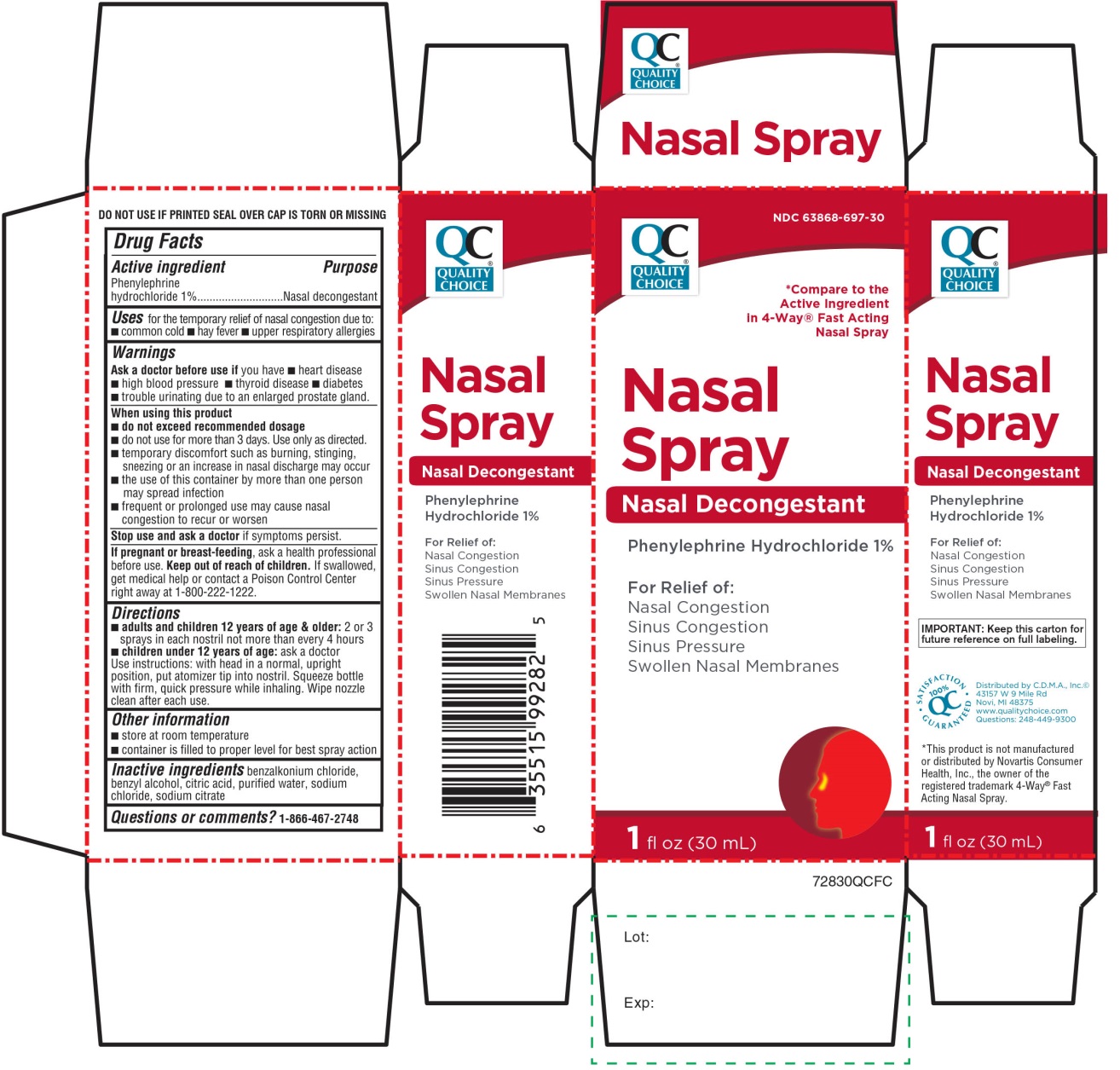 DRUG LABEL: Quality Choice
NDC: 63868-697 | Form: SOLUTION/ DROPS
Manufacturer: CHAIN DRUG MARKETING ASSOCIATION
Category: otc | Type: HUMAN OTC DRUG LABEL
Date: 20251204

ACTIVE INGREDIENTS: PHENYLEPHRINE HYDROCHLORIDE 1 g/100 mL
INACTIVE INGREDIENTS: BENZALKONIUM CHLORIDE; BENZYL ALCOHOL; ANHYDROUS CITRIC ACID; WATER; SODIUM CHLORIDE; SODIUM CITRATE, UNSPECIFIED FORM

Quality Choice Nasal Spray Phenylephrine HCl Drug Facts

Active ingredient

Phenylephrine hydrochloride 1%

Purpose

Nasal decongestant

Uses

for the temporarily relief nasal congestion due to:

- common cold
- hay fever
- upper respiratory allergies

Warnings

Ask a doctor before use if you have

- heart disease
- high blood pressure
- thyroid disease
- diabetes
- trouble urinating due to an enlarged prostate gland

When using this product

- do not use more than directed
- do not use for more than 3 days. Use only as directed. Frequent or prolonged use may cause nasal congestion to recur or worsen.
- temporary discomfort such as burning, stinging, sneezing, or an increase in nasal discharge may occur
- use of this container by more than one person may spread infection

Stop use and ask a doctor if

symptoms persist

If pregnant or breast-feeding,

ask a health professional before use.

Keep out of reach of children.

If swallowed, get medical help or contact a Poison Control Center right away (1-800-222-1222).

Directions

- adults and children 12 years of age and older:2 or 3 drops in each nostril not more often than every 4 hours
- children under 12 years of age:ask a doctor

Use instructions: with head in a normal, upright position, put atomizer tip into nostril. Squeeze bottle with firm, quick pressure while inhaling. Wipe nozzle clean after each use.

Other information

- store at room temperature
- container is filled to proper level for best spray action.

Inactive ingredients

benzalkonium chloride, benzyl alcohol, citric acid, purified water, sodium chloride, sodium citrate

Questions or comments?

1-866-467-2748

Principal Display Panel

NDC# 63868-697-30

*Compare to Active Ingredient in 4-Way®Fast Acting Nasal Spray

Nasal Spray

Nasal Decongestant

PHENYLEPHRINE HCl 1%

For Relief of:

Nasal Congestion

Sinus Congestion

Sinus Pressure

Swollen Nasal Membranes

100% QC SATISFACTION GUARANTEED

1 FL OZ (30 mL)

Distributed by: C.D.M.A. Inc. ©

43157 W 9 Mile Rd

Novi, MI 48375

www.qualitychoice.com

Questions: 248-449-9300

*This product is not manufactured or distributed by Novartis Consumer Health, Inc. the owner of the registered trademark 4-Way®Fast Acting Nasal Spray.